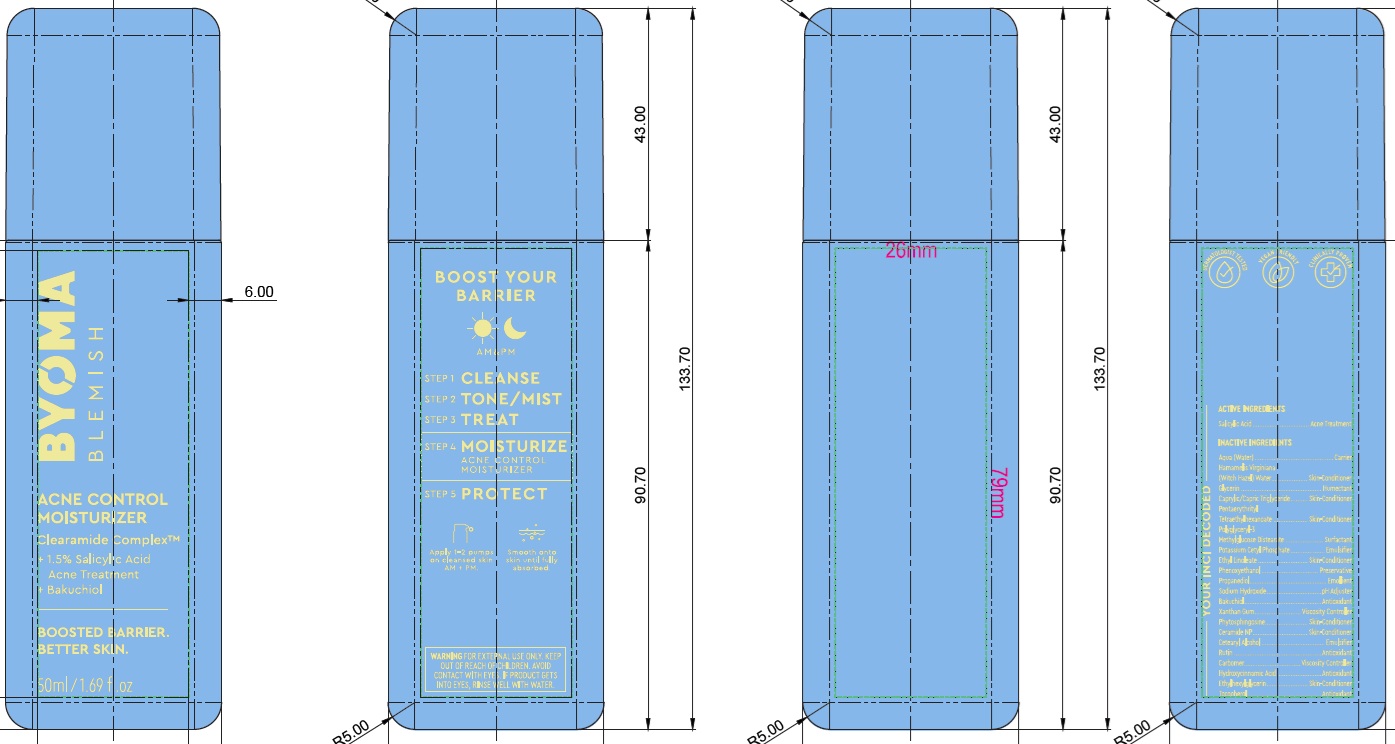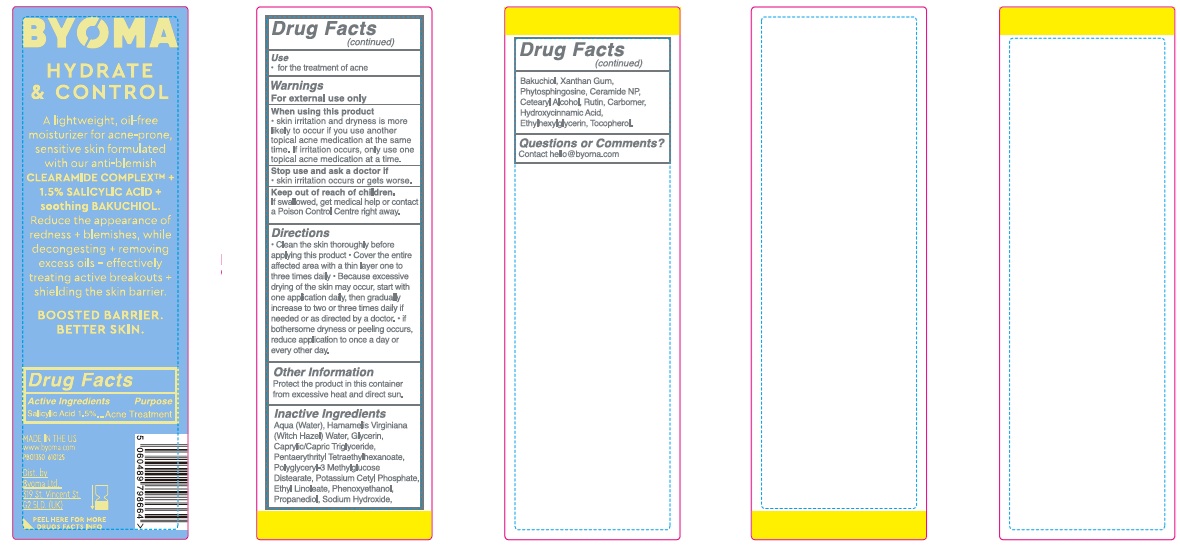 DRUG LABEL: Byoma Acne Control Moisturizer
NDC: 84821-006 | Form: LOTION
Manufacturer: Byoma Ltd
Category: otc | Type: HUMAN OTC DRUG LABEL
Date: 20250423

ACTIVE INGREDIENTS: SALICYLIC ACID 15 mg/1 mL
INACTIVE INGREDIENTS: CAPRYLIC/CAPRIC TRIGLYCERIDE; ETHYL LINOLEATE; CARBOMER; HYDROXYCINNAMIC ACID; GLYCERIN; POTASSIUM CETYL PHOSPHATE; BAKUCHIOL; CERAMIDE NP; ETHYLHEXYLGLYCERIN; WATER; PHENOXYETHANOL; HAMAMELIS VIRGINIANA TOP WATER; POLYGLYCERYL-3 METHYLGLUCOSE DISTEARATE; PROPANEDIOL; SODIUM HYDROXIDE; XANTHAN GUM; RUTIN; TOCOPHEROL; PENTAERYTHRITYL TETRAETHYLHEXANOATE; PHYTOSPHINGOSINE; CETEARYL ALCOHOL

Byoma Acne Control Moisturizer

Active Ingredients

Salicylic Acid 1.5%

Purpose

Acne Treatment

Use

- for the treatment of acne

Warnings

For external use only

When using this product

- skin irritation and dryness is more likely to occur if you use another topical acne medication at the same time. If irritation occurs, only use one topical acne medication at a time.

Stop use and ask a doctor if

- skin irritation occurs or gets worse.

Keep out of reach of children.

If swallowed, get medical help or contact a Poison Control Centre right away.

Directions

- Clean the skin thoroughly before applying this product
- Cover the entire affected area with a thin layer one to three times daily.
- Because excessive drying of the skin may occur, start with one application daily, then gradually increase to two or three times daily if needed or as directed by a doctor.
- If bothersome dryness or peeling occurs, reduce application to once a day or every other day.

Other Information

Protect the product in this container from excessive heat and direct sun.

Inactive Ingredients

Aqua (Water), Hamamelis Virginiana (Witch Hazel) Water, Glycerin, Caprylic/Capric Triglyceride, Pentaerythrityl Tetraethylhexanoate, Polyglyceryl-3 Methylglucose Distearate, Potassium Cetyl Phosphate, Ethyl Linoleate, Phenoxyethanol, Propanediol, Sodium Hydroxide, Bakuchiol, Xanthan Gum, Phytosphingosine, Ceramide NP, Cetearyl Alcohol, Rutin, Carbomer, Hydroxycinnamic Acid, Ethylhexylglycerin, Tocopherol.

Questions or Comments?

Contact hello@byoma.com